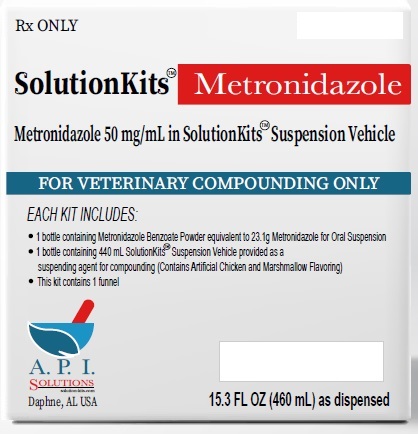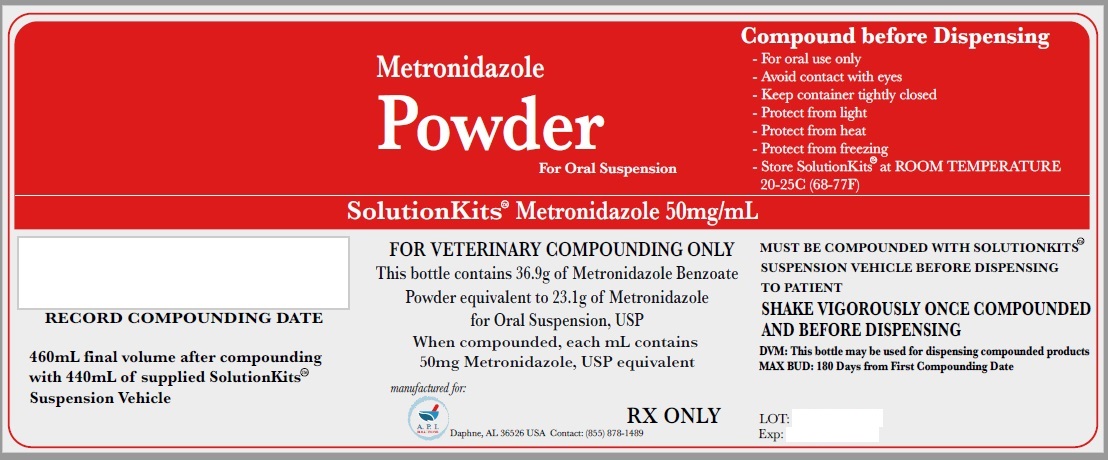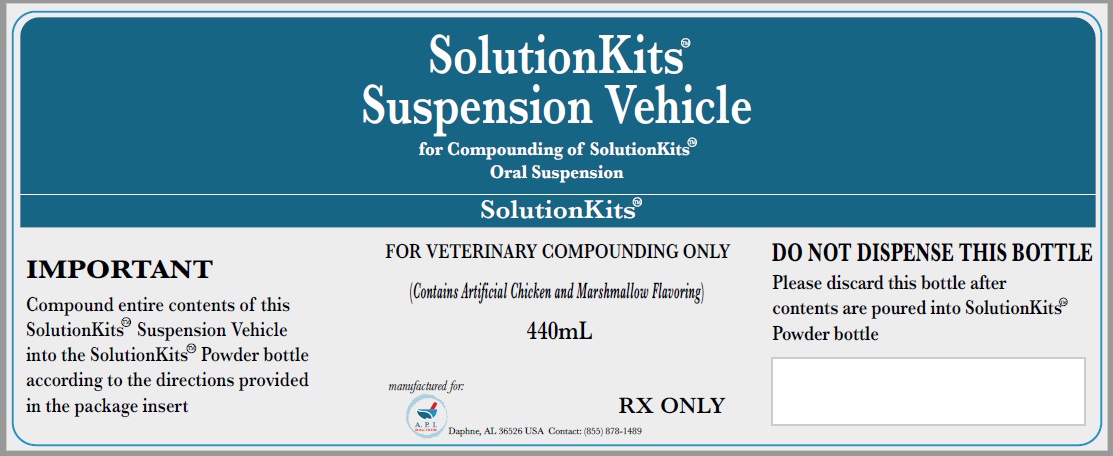 DRUG LABEL: SolutitionKits
NDC: 46144-602 | Form: KIT | Route: NOT APPLICABLE
Manufacturer: API Solutions
Category: other | Type: BULK INGREDIENT - ANIMAL DRUG
Date: 20260120

ACTIVE INGREDIENTS: METRONIDAZOLE BENZOATE 1 g/1 g
INACTIVE INGREDIENTS: .ALPHA.-TOCOPHEROL; MEDIUM-CHAIN TRIGLYCERIDES; AMMONIUM GLYCYRRHIZATE; COCONUT OIL; BUTYLATED HYDROXYANISOLE; POLYGLYCERYL-3 OLEATE; SILICON DIOXIDE

SolutionsKits Metronidazole Benzoate USP

SolutionKits™Metronidazole

Metronidazole 50 mg/mL in SolutionKits™ Suspension Vehicle

FOR VETERINARY COMPOUNDING ONLY

Each kit includes:

1 bottle containing Metronidazole Benzoate Powder equivalent to 23.1g Metronidazole for Oral Suspension

1 bottle containing 440 mL SolutionKits™ Suspension Vehicle provided as a suspending agent for compounding (Contains Artificial Chicken and Marshmallow Flavoring)

This kit contains 1 funnel

A.P.I.

Solutions

Daphne, AL USA

15.3 FL OZ (460 mL) as dispensed